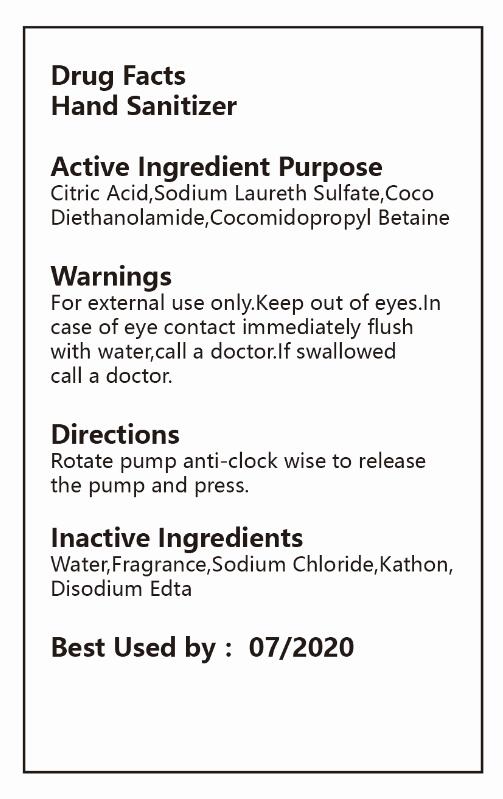 DRUG LABEL: HAND SANITIZER
NDC: 47993-204 | Form: LIQUID
Manufacturer: NINGBO JIANGBEI OCEAN STAR TRADING CO.,LTD
Category: otc | Type: HUMAN OTC DRUG LABEL
Date: 20171206

ACTIVE INGREDIENTS: CITRIC ACID MONOHYDRATE 0.3 g/100 g; COCAMIDOPROPYL BETAINE 5 1/100 g
INACTIVE INGREDIENTS: SODIUM LAURETH SULFATE 15 g/100 g; COCO DIETHANOLAMIDE 6 g/100 g; EDETIC ACID 1 g/100 g; SODIUM CHLORIDE 2 g/100 g; AROMADENDRIN 0.2 g/100 g; ISOTHIAZOLINONE 0.3 g/100 g; WATER 70.2 1/100 g

Active Ingredients

Active ingredients--------------purpose

Citric Acid，Sodium Laureth Sulfate，Coco Diethanolamide，Cocomidopropyl Betaine

Uses:
Reduces bacteria on the skin. Recommended for repeated use.

Warnings:

For external use only.Keep out of eyes.In case of eye contact immediately flush with water,call a doctor.If swallowed call a doctor.

Directions:

Rotate pump anti-clock wise to release the pump and press.

Other Information

Do not store above 110F(43C) May discolor certain fabric or surfaces. Harmful to wood finishes and plastics.

KEEP OUT OF REACH OF CHILDREN

Children under 6 years of age should be super vised when using this product.

Inactive Ingredients:

Water,Fragrance,Sodium Chloride,Kathon,Disodium Edta